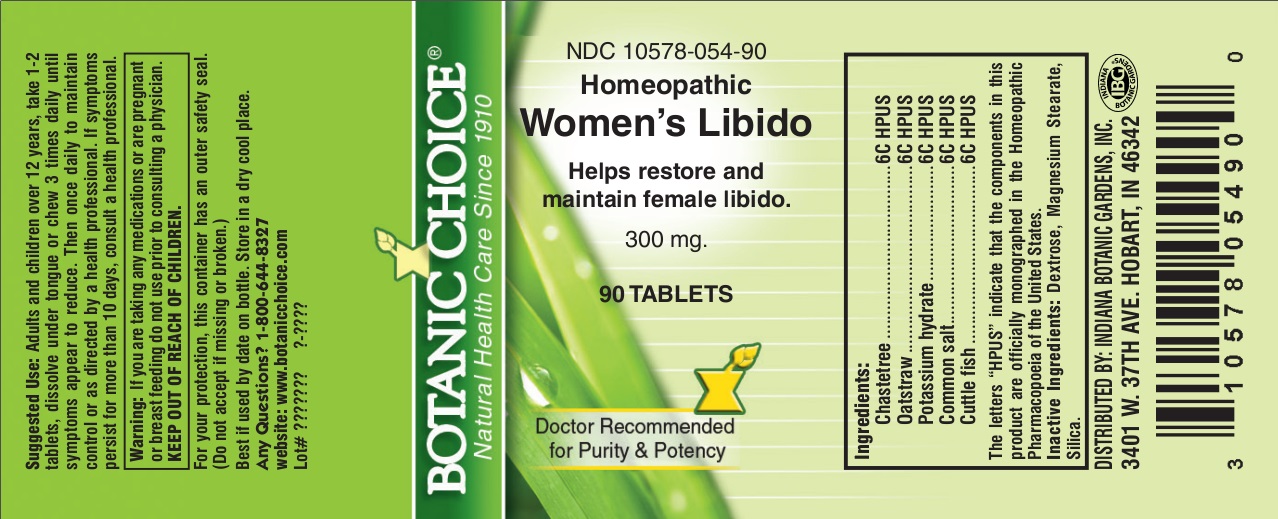 DRUG LABEL: Homeopathic Womens Libido
NDC: 10578-054 | Form: TABLET
Manufacturer: Indiana Botanic Gardens
Category: homeopathic | Type: HUMAN OTC DRUG LABEL
Date: 20140926

ACTIVE INGREDIENTS: CHASTE TREE 6 [hp_C]/1 1; AVENA SATIVA FLOWERING TOP 6 [hp_C]/1 1; CAUSTICUM 6 [hp_C]/1 1; SODIUM CHLORIDE 6 [hp_C]/1 1; SEPIA OFFICINALIS JUICE 6 [hp_C]/1 1
INACTIVE INGREDIENTS: DEXTROSE; MAGNESIUM STEARATE; SILICON DIOXIDE

Homeopathic Womens Libido

Suggested Use:

Adults and children over 12 years, take 1-2 tablets, dissolve under tongue or chew 3 times daily until symptoms appear to reduce. Then once daily to maintain control or as directed by a health professional.

STOP USE

If symptoms persist for more than 10 days, consult a health professional.

Warning:

If you are taking any medications or are pregnant or breast feeding do not use prior to consulting a physician.

KEEP OUT OF REACH OF CHILDREN.

For your protection, this container has an outer safety seal.

(Do not accept if missing or broken.)

Best if used by date on bottle. Store in a dry cool place.

Any Questions?

1-800-644-8327

website: www.botanicchoice.com

INDICATIONS AND USAGE

Helps restore and maintain female libido.

PURPOSE

Helps restore and maintain female libido.

Ingredients:

Chastetree ....................................6C HPUS

Oatstraw .......................................6C HPUS

Potassium hydrate ........................6C HPUS

Common salt .................................6C HPUS

Cuttle fish .....................................6C HPUS

The letters "HPUS" indicate that the components in this product are officially monographed in the Homeopathic Pharmacopoeia of the United States.

Inactive Ingredients:

Dextrose, Magnesium Stearate, Silica.

DISTRIBUTED BY: INDIANA BOTANIC GARDENS, INC.

3401 W. 37TH AVE. HOBART, IN 46342

Botanic Choice

Natural Health Care Since 1910

NDC 10578-054-90

Homeopathic Women's Libido

Helps restore and maintain female libido.

300 mg.

90 TABLETS